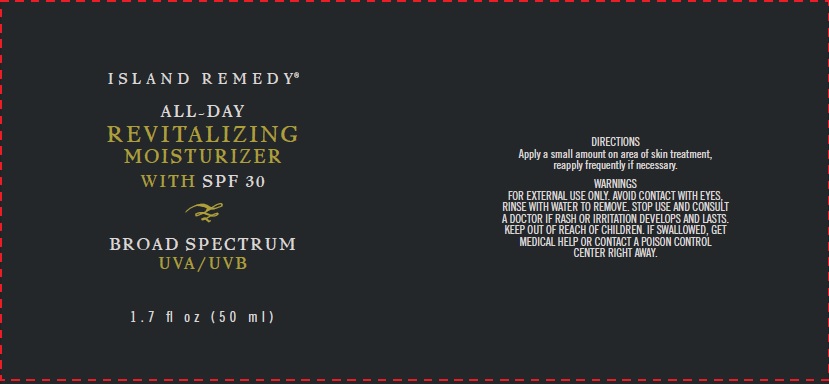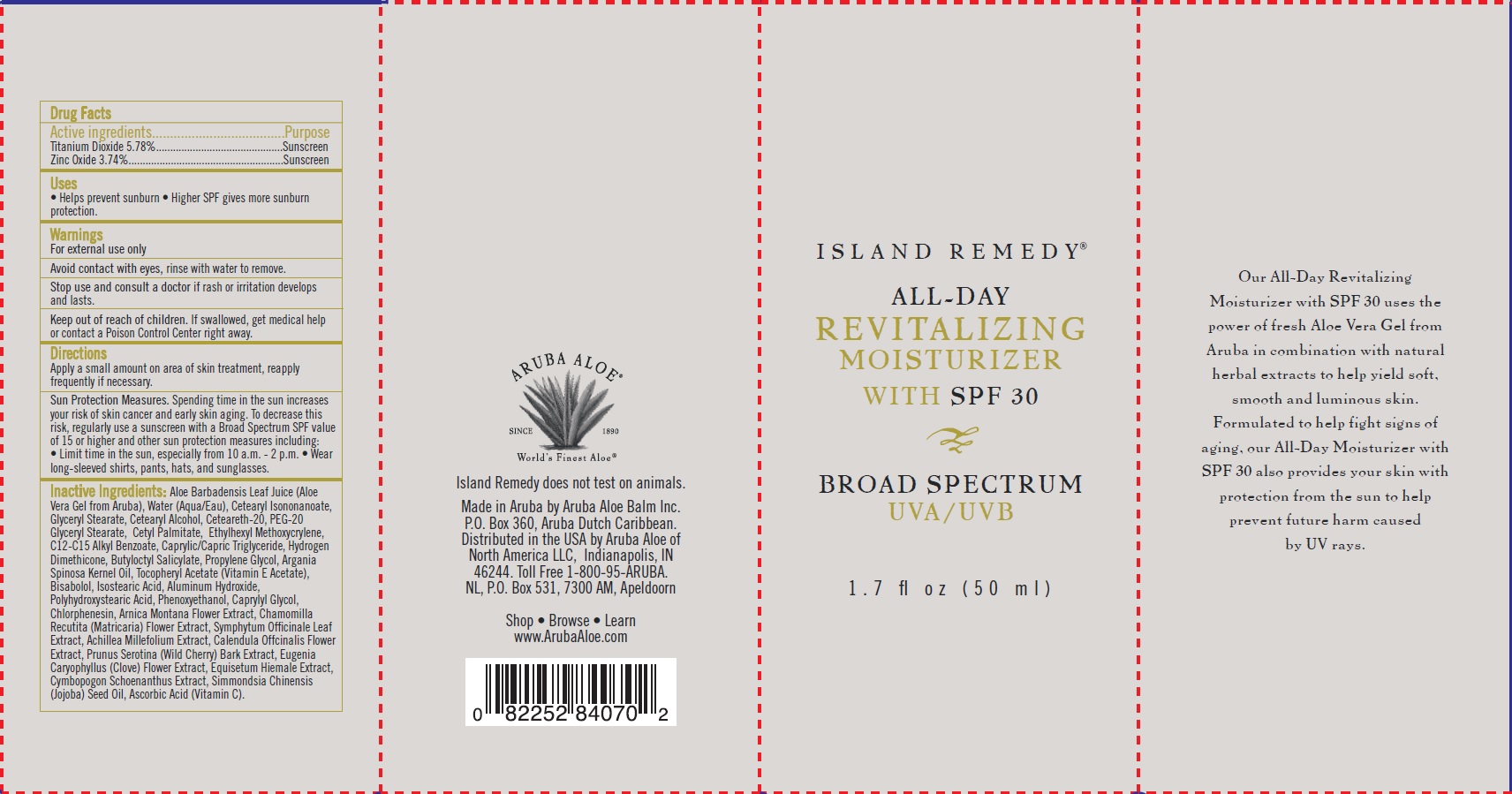 DRUG LABEL: Island Remedy All-day Revitalizing Moisturizer with SPF 30
NDC: 53675-160 | Form: CREAM
Manufacturer: Aruba Aloe Balm NV
Category: otc | Type: HUMAN OTC DRUG LABEL
Date: 20231106

ACTIVE INGREDIENTS: TITANIUM DIOXIDE 57.8 mg/1 mL; ZINC OXIDE 37.4 mg/1 mL
INACTIVE INGREDIENTS: ALOE VERA LEAF; WATER; CETEARYL ISONONANOATE; GLYCERYL MONOSTEARATE; CETOSTEARYL ALCOHOL; POLYOXYL 20 CETOSTEARYL ETHER; PEG-20 GLYCERYL STEARATE; CETYL PALMITATE; ETHYLHEXYL METHOXYCRYLENE; ALKYL (C12-15) BENZOATE; MEDIUM-CHAIN TRIGLYCERIDES; BUTYLOCTYL SALICYLATE; PROPYLENE GLYCOL; ARGAN OIL; .ALPHA.-TOCOPHEROL ACETATE; LEVOMENOL; ISOSTEARIC ACID; ALUMINUM HYDROXIDE; POLYHYDROXYSTEARIC ACID (2300 MW); PHENOXYETHANOL; CAPRYLYL GLYCOL; CHLORPHENESIN; ARNICA MONTANA FLOWER; CHAMOMILE; COMFREY LEAF; ACHILLEA MILLEFOLIUM; CALENDULA OFFICINALIS FLOWER; PRUNUS SEROTINA BARK; CLOVE; EQUISETUM HYEMALE; CYMBOPOGON SCHOENANTHUS TOP; JOJOBA OIL; ASCORBIC ACID

Island Remedy All-day Revitalizing Moisturizer with SPF 30

Active ingredients

Titanium Dioxide 5.78%

Zinc Oxide 3.74%

Purpose

Sunscreen

Uses

• Helps prevent sunburn • Higher SPF gives more sunburn protection.

Warnings

For external use only

Avoid contact with eyes, rinse with water to remove.

Stop use and consult a doctor

if rash or irritation develops and lasts.

Keep out of reach of children.

If swallowed, get medical help or contact a Poison Control Center right away.

Directions

Apply a small amount on area of skin treatment, reapply frequently if necessary.

Sun Protection Measures. Spending time in the sun increases your risk of skin cancer and early skin aging. To decrease this risk, regularly use a sunscreen with a Broad Spectrum SPF value of 15 or higher and other sun protection measures including: • Limit time in the sun, especially from 10 a.m. - 2 p.m. • Wear long-sleeved shirts, pants, hats, and sunglasses.

Inactive Ingredients:

Aloe Barbadensis Leaf Juice (Aloe Vera Gel from Aruba), Water (Aqua/Eau), Cetearyl Isononanoate, Glyceryl Stearate, Cetearyl Alcohol, Ceteareth-20, PEG-20 Glyceryl Stearate, Cetyl Palmitate, Ethylhexyl Methoxycrylene, C12-C15 Alkyl Benzoate, Caprylic/Capric Triglyceride, Hydrogen Dimethicone, Butyloctyl Salicylate, Propylene Glycol, Argania Spinosa Kernel Oil, Tocopheryl Acetate (Vitamin E Acetate), Bisabolol, Isostearic Acid, Aluminum Hydroxide, Polyhydroxystearic Acid, Phenoxyethanol, Caprylyl Glycol, Chlorphenesin, Arnica Montana Flower Extract, Chamomilla Recutita (Matricaria) Flower Extract, Symphytum Officinale Leaf Extract, Achillea Millefolium Extract, Calendula Offcinalis Flower Extract, Prunus Serotina (Wild Cherry) Bark Extract, Eugenia Caryophyllus (Clove) Flower Extract, Equisetum Hiemale Extract, Cymbopogon Schoenanthus Extract, Simmondsia Chinensis (Jojoba) Seed Oil, Ascorbic Acid (Vitamin C).

Package Labeling:

Inner Package Labeling:

Outer Package Labeling: